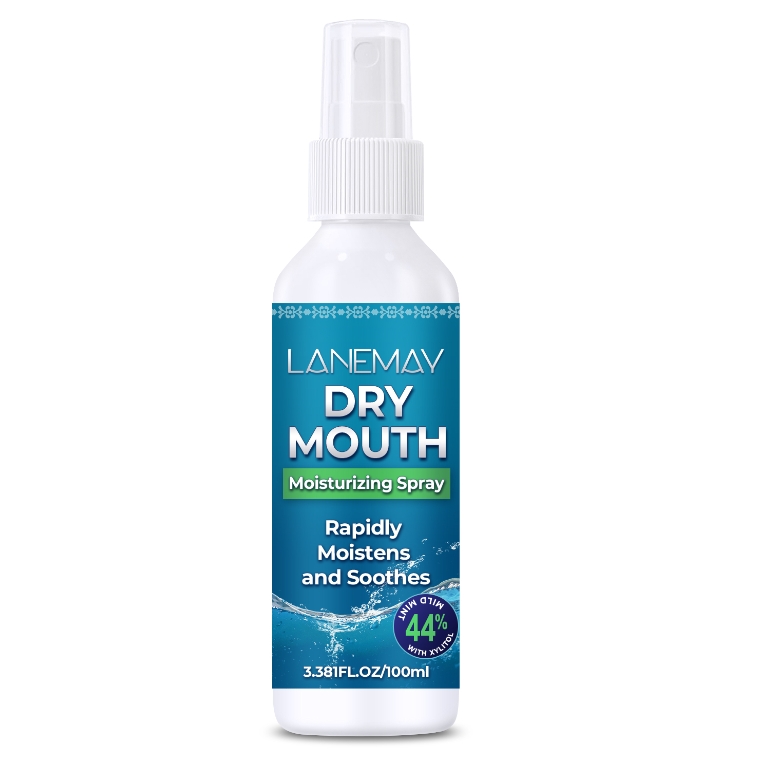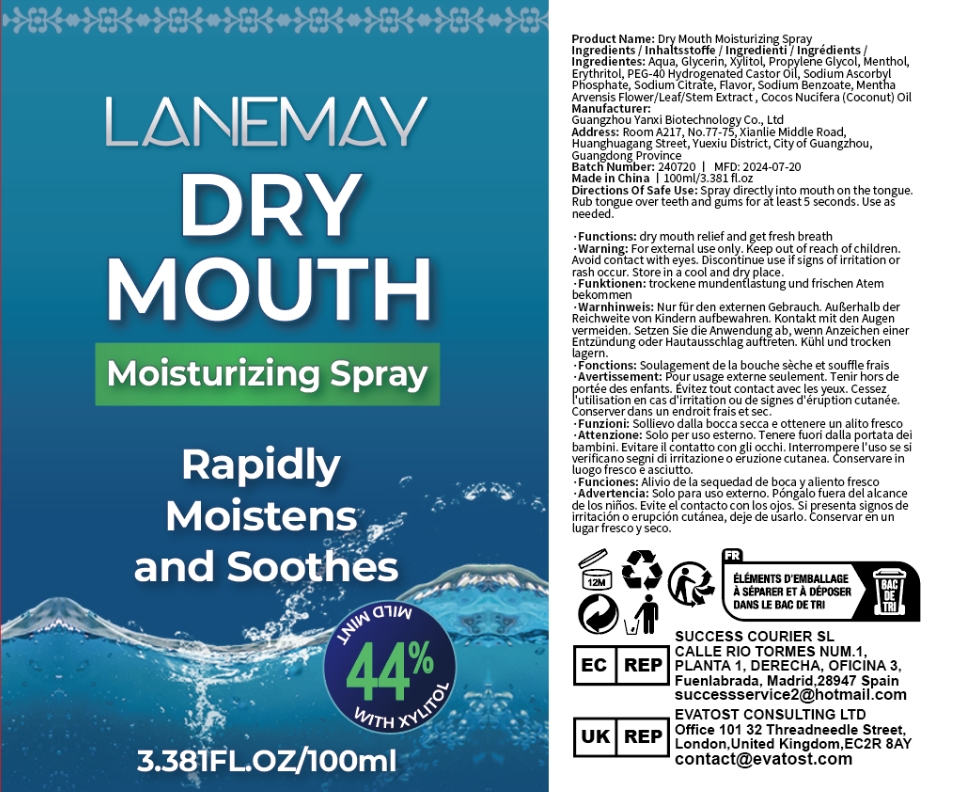 DRUG LABEL: Dry Mouth MoisturizingSpray
NDC: 84025-098 | Form: SPRAY
Manufacturer: Guangzhou Yanxi Biotechnology Co., Ltd
Category: otc | Type: HUMAN OTC DRUG LABEL
Date: 20240729

ACTIVE INGREDIENTS: GLYCERIN 3 mg/100 mL; MENTHOL 5 mg/100 mL
INACTIVE INGREDIENTS: WATER

DOSAGE AND ADMINISTRATION

Spray directly into mouth on the tongue.

WARNINGS

keep put of children

INACTIVE INGREDIENT

Aqua

INDICATIONS AND USAGE

dry mouth

keep put of chlidren

PURPOSE

trockene mundenflastung und frischen Atem bekommen